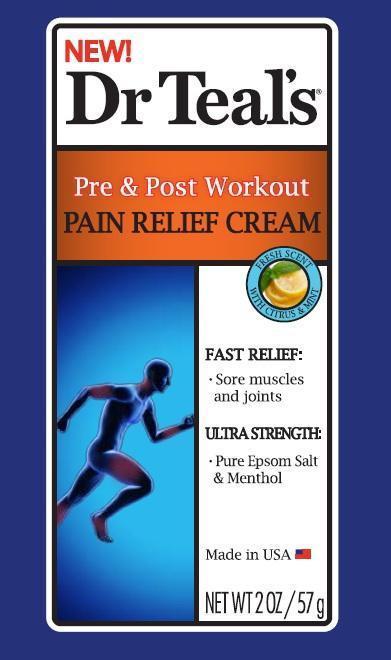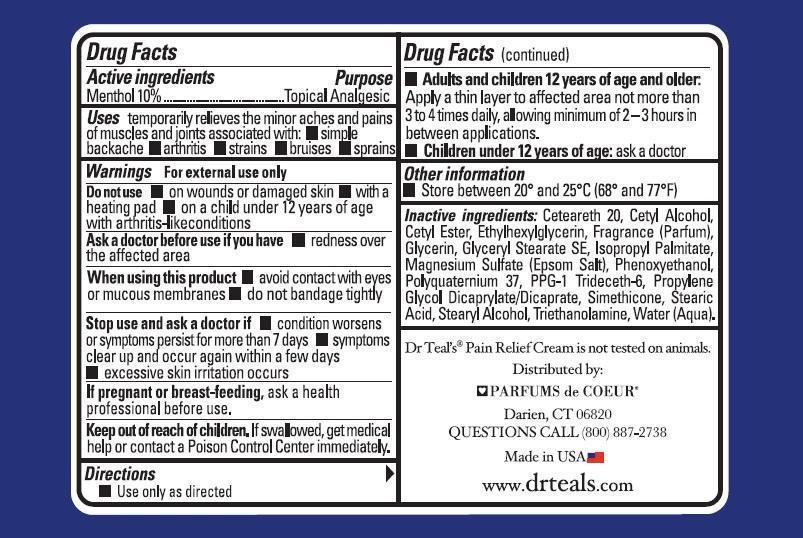 DRUG LABEL: Dr. Teals
NDC: 61012-010 | Form: CREAM
Manufacturer: PDC Brands
Category: otc | Type: HUMAN OTC DRUG LABEL
Date: 20151228

ACTIVE INGREDIENTS: MENTHOL 100 mg/1 g
INACTIVE INGREDIENTS: CETYL ESTERS WAX; ETHYLHEXYLGLYCERIN; GLYCERIN; GLYCERYL STEARATE SE; ISOPROPYL PALMITATE; MAGNESIUM SULFATE; PHENOXYETHANOL; POLYQUATERNIUM 37 (200 MPA.S); PPG-1 TRIDECETH-6; PROPYLENE GLYCOL DICAPRYLATE/DICAPRATE; DIMETHICONE; STEARIC ACID; STEARYL ALCOHOL; TROLAMINE; WATER; POLYOXYL 20 CETOSTEARYL ETHER; CETYL ALCOHOL

Dr. Teal's Pre and Post Workout Pain Relief Cream

Drug Facts

Active ingredients

Menthol 10%

Purpose

Topical Analgesic

Uses

Temporarily relieves the minor aches and pains of muscles and joints associated with:

- simple backache
- arthritis
- strains
- bruises
- sprains

Warnings

For external use only

Do not use

- on wounds or damaged skin
- with a heating pad
- on a child under 12 years of age with arthritis-like conditions

Ask a doctor before use if you have

- redness over the affected area

When using this product

- avoid contact with eyes or mucous membranes
- do not bandage tightly

Stop use and ask a doctor if

- condition worsens or symptoms persist for more than 7 days
- symptoms clear up and occur again within a few days
- excessive skin irritation occurs

If pregnant or breast-feeding,

ask a health professional before use.

Keep out of reach of children.

If swallowed, get medical help or contact a Poison Control Center immediately.

Directions

- Use only as directed
- Adults and children 12 years of age and older:

Apply a thin layer to affected area not more than 3 to 4 times daily, allowing minimum of 2-3 hours in between applications.

- Children under 12 years of age: ask a doctor

Other information

- Store between 20° and 25°C (68° and 77°F)

Inactive ingredients:

Cetearath 20, Cetyl Alcohol, Cetyl Ester, Ethylhexylglycerin, Fragrance(Parfum), Glycerin, Glyceryl Stearate SE, Isopropyl Palmitate, Magnesium Sulfate (Epsom Salt), Phenoxyethanol, Polyquaternium 37, PPG-1 Trideceth-6, Propylene Glycol Dicaprylate/Dicaprate, Simethicone, Stearic Acid, Stearyl Alcohol, Triethanolamine, Water (Aqua).

Principal Display Panel Dr. Teal's Pre & Post Workout Pain Relief Cream 2 oz./57g NDC: 61012-010-57

Label1.jpg Label2.jpg